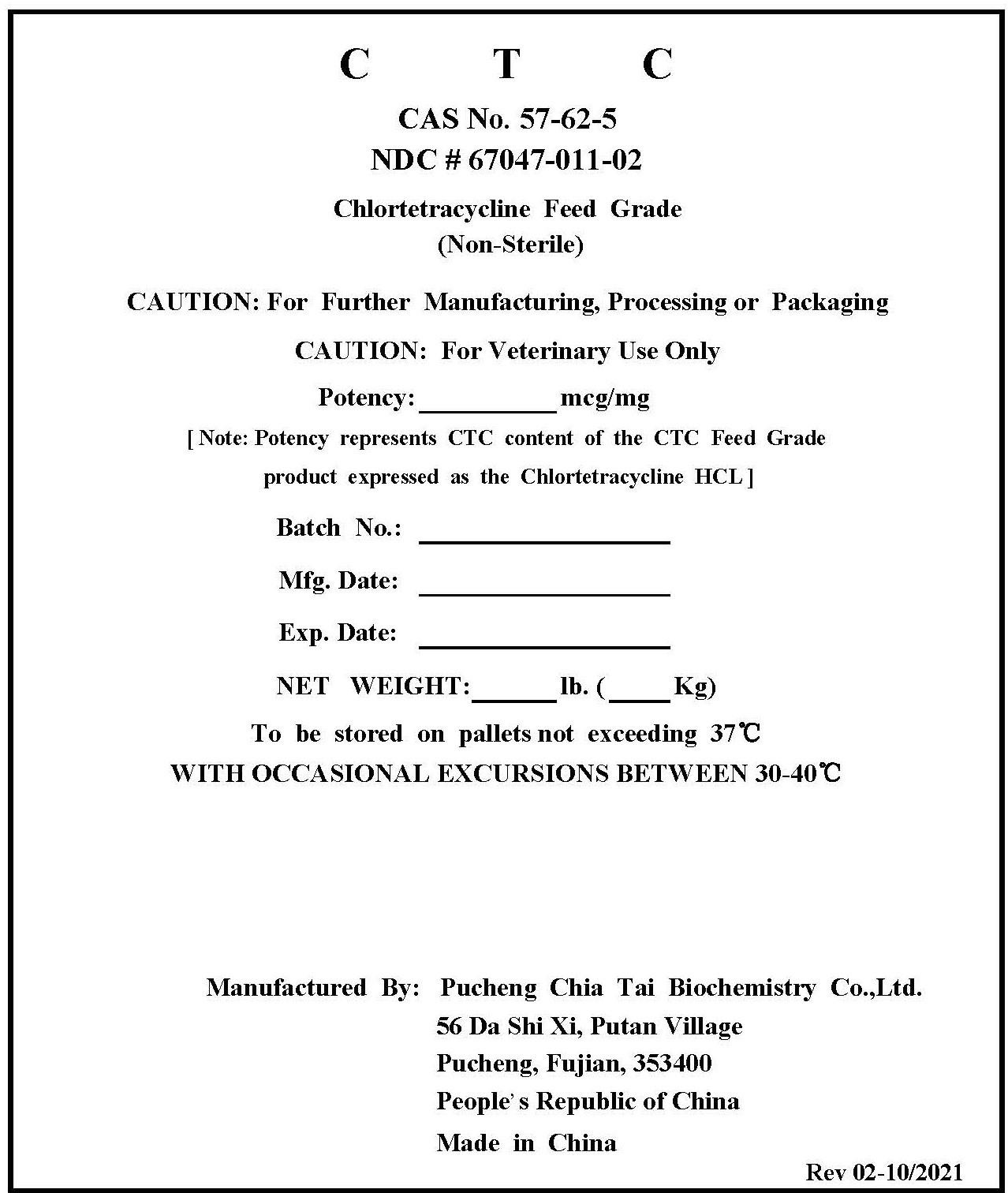 DRUG LABEL: Chlortetracycline Feed Grade
NDC: 67047-011 | Form: POWDER
Manufacturer: Pucheng Chia Tai Biochemistry Co. Ltd.
Category: other | Type: BULK INGREDIENT - ANIMAL DRUG
Date: 20211022

ACTIVE INGREDIENTS: Chlortetracycline Calcium 1 kg/1 kg

Chlortetracycline Feed Grade

PACKAGE LABEL

C T C

CAS No. 57-62-5
NDC # 67047-011-02

Chlortetracycline Feed Grade
(Non-Sterile)

CAUTION: For Further Manufacturing, Processing or Packaging
CAUTION: For Veterinary Use Only
Potency: ________ mcg/mg
[ Note: Potency represents CTC content of the CTC Feed Grade
product expressed as the Chlortetracycline HCL ]
Batch No.: ________________
Expiration Date: ___________
NET WEIGHT: ______ lb. (_____ Kg)
To be stored on pallets not exceeding 37°C
WITH OCCASIONAL EXCURSIONS BETWEEN 30-40°C

Manufactured By:

Pucheng Chia Tai Biochemistry Co.,Ltd.
56 Da Shi Xi, Putan Village
Pucheng, Fujian, 353400
People' s Republic of China
Made in China

Rev 02-10/2021